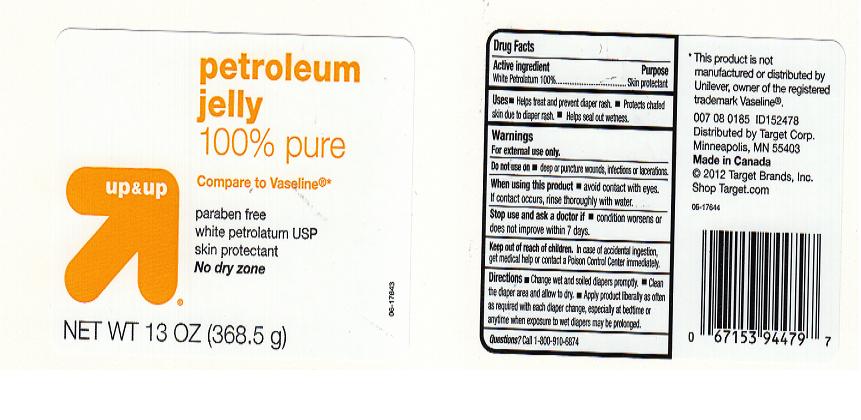 DRUG LABEL: UP and UP
NDC: 11673-350 | Form: JELLY
Manufacturer: TARGET CORPORATION
Category: otc | Type: HUMAN OTC DRUG LABEL
Date: 20111216

ACTIVE INGREDIENTS: PETROLATUM 99.9 g/100 g
INACTIVE INGREDIENTS: PETROLATUM

DRUG FACTS

ACTIVE INGREDIENT

WHITE PETROLATUM 100%

PURPOSE

SKIN PROTECTANT

USES

HELPS TREAT AND PREVENT DIAPER RASH. PROTECTS CHAFED SKIN DUE TO DIAPER RASH. HELPS SEAL OUT WETNESS

WARNINGS

FOR EXTERNAL USE ONLY

DO NOT USE ON

DEEP OR PUNCTURE WOUNDS, INFECTIONS OR LACERATIONS

WHEN USING THIS PRODUCT

AVOID CONTACT WITH EYES. IF CONTACT OCCURS, RINSE THOROUGHLY WITH WATER.

STOP USE AND ASK DOCTOR IF

CONDITION WORSENS, OR DOES NOT IMPROVE WITHIN 7 DAYS.

KEEP OUT OF REACH OF CHILDREN

IN CASE OF ACCIDENTAL INGESTION, GET MEDICAL HELP OR CONTACT A POISON CONTROL CENTER IMMEDIATELY

DIRECTIONS

CHANGE WET AND SOILED DIAPERS PROMPTLY. CLEAN THE DIAPER AREA AND ALLOW TO DRY. APPLY PRODUCT LIBERALLY AS OFTEN AS REQUIRED WITH EACH DIAPER CHANGE, ESPECIALLY AT BED TIME OR ANYTIME WHEN EXPOSURE TO WET DIAPER MAY BE PROLONGED.

QUESTIONS?

CALL 1-800-910-6874

INACTIVE INGREDIENT

PETROLATUM